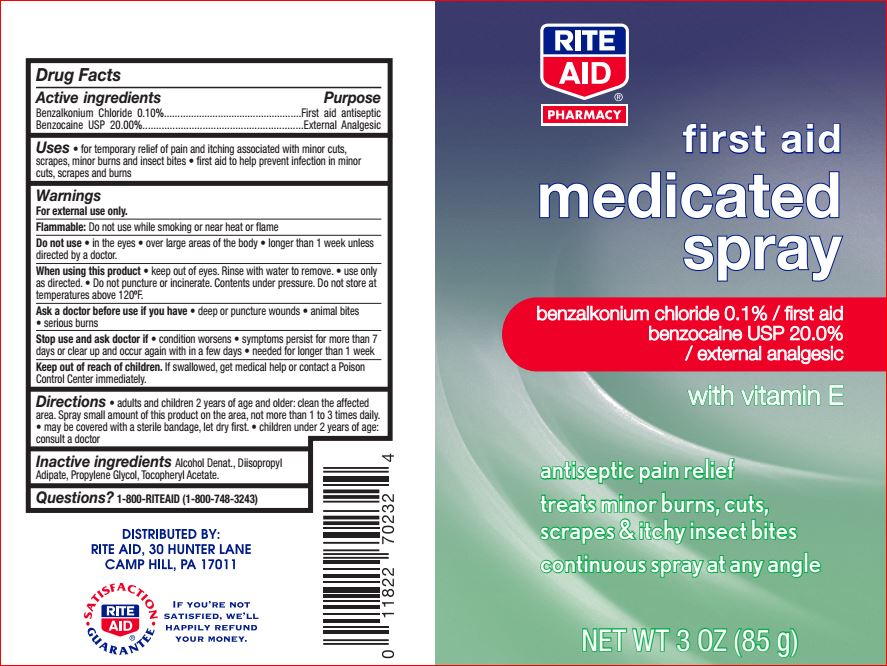 DRUG LABEL: First Aid Medicated
NDC: 11822-7801 | Form: SPRAY
Manufacturer: Rite Aid
Category: otc | Type: HUMAN OTC DRUG LABEL
Date: 20180606

ACTIVE INGREDIENTS: Benzalkonium Chloride 0.1 g/100 g; BENZOCAINE 20 g/100 g
INACTIVE INGREDIENTS: Alcohol; Diisopropyl Adipate; Propylene Glycol; .ALPHA.-TOCOPHEROL ACETATE

Drug Facts

Active ingredients Purpose
Benzalkonium Chloride 0.10%...................................................First aid antiseptic
Benzocaine USP 20.00%...........................................................External Analgesic

INDICATIONS AND USAGE

Uses • for temporary relief of pain and itching associated with minor cuts,
scrapes, minor burns and

Warnings
For external use only.
Flammable: Do not use while smoking or near heat or flame
Do not use • in the eyes • over large areas of the body • longer than 1 week unless
directed by a doctor.
When using this product • keep out of eyes. Rinse with water to remove. • use only
as directed. • Do not puncture or incinerate. Contents under pressure. Do not store at
temperatures above 120ºF.
Ask a doctor before use if you have • deep or puncture wounds • animal bites
• serious burns
Stop use and ask doctor if • condition worsens • symptoms persist for more than 7
days or clear up and occur again with in a few days • needed for longer than 1 week

Keep out of reach of children. If swallowed, get medical help or contact a Poison
Control Center immediately.

DOSAGE AND ADMINISTRATION

Directions • adults and children 2 years of age and older: clean the affected
area. Spray small amount of this product on the area, not more than 1 to 3 times daily.
• may be covered with a sterile bandage, let dry first. • children under 2 years of age:
consult a doctor

Inactive ingredients

Alcohol Denat., Diisopropyl
Adipate, Propylene Glycol, Tocopheryl Acetate.